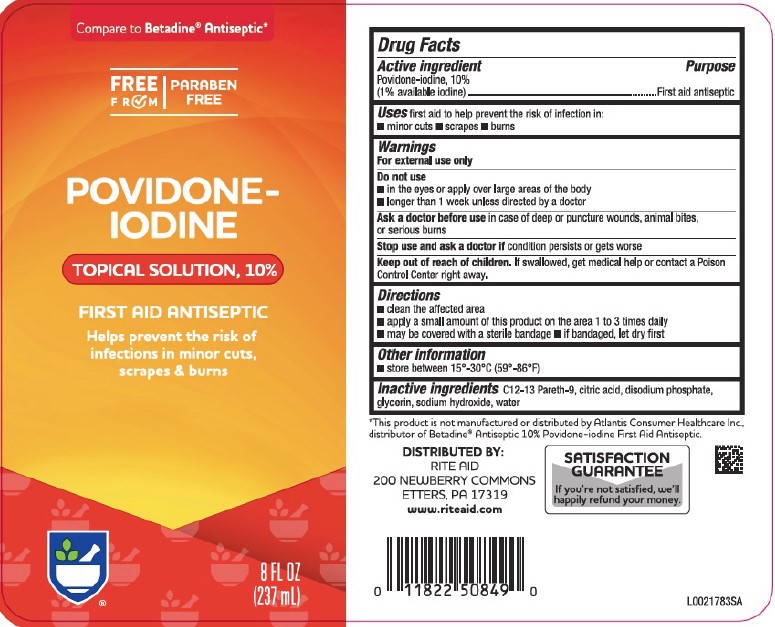 DRUG LABEL: First Aid Antiseptic
NDC: 11822-9050 | Form: SOLUTION
Manufacturer: Rite Aid Corporation
Category: otc | Type: HUMAN OTC DRUG LABEL
Date: 20260130

ACTIVE INGREDIENTS: POVIDONE-IODINE 10 mg/1 mL
INACTIVE INGREDIENTS: C12-13 PARETH-9; CITRIC ACID MONOHYDRATE; SODIUM PHOSPHATE, DIBASIC, ANHYDROUS; GLYCERIN; SODIUM HYDROXIDE; WATER

Rite Aid 050.002/050AE
Povidone Iodine Solution

Active ingredient

Povidone-iodine, 10% (1% available iodine)

Purpose

First aid antiseptic

Uses

first aid to help prevent the risk of infection in:

- minor cuts
- scrapes
- burns

Warnings

For external use only

Do not use

- in the eyes or apply over large areas of the body
- longer than 1 week unless directed by a doctor

Ask a doctor before use

in case of deep or puncture counds, animal bites, or serious burns

Stop use and ask a doctor if

condition persists or gets worse

Keep out of reach of children.

If swallowed, get medical help or contact a Poison Control Center right away.

Directions

- clean the affected area
- apply a small amount of this product on the area 1 to 3 times daily
- may be covered with a sterile bandage.
- if bandaged, let dry first.

Other inforamation

- store between 15º-30ºC (59º-86ºF)

inactive ingredents

C12-13 Pareth-9, citric acid, disodium phosphate, glycerin, sodium hydroxide, water

Disclaimer

*This product is not manufactured or distributed by Atlantis Consumer Healthcare Inc., distributor of BetadineAntiseptic 10% Povidone-iodine First Aid Antiseptic.

Adverse Reactions

DISTRIBUTED BY:

RITE AID

200 NEWBERRY COMMONS

ETTERS, PA 17319

www.riteaid.com

SATISFACTION GUARANTEE

If you're not satisfied, we'll happily refund your money.

principal display panel

Compare to Betadine®Antiseptic*

FREE FROM

PARABEN FREE

POVIDONE-IODINE

TOPICAL SOLUTION, 10%

FIRST AID ANTISEPTIC

Helps prevent the risk of infections in minor cuts, scrapes & burns

8 FL OZ (237 mL)